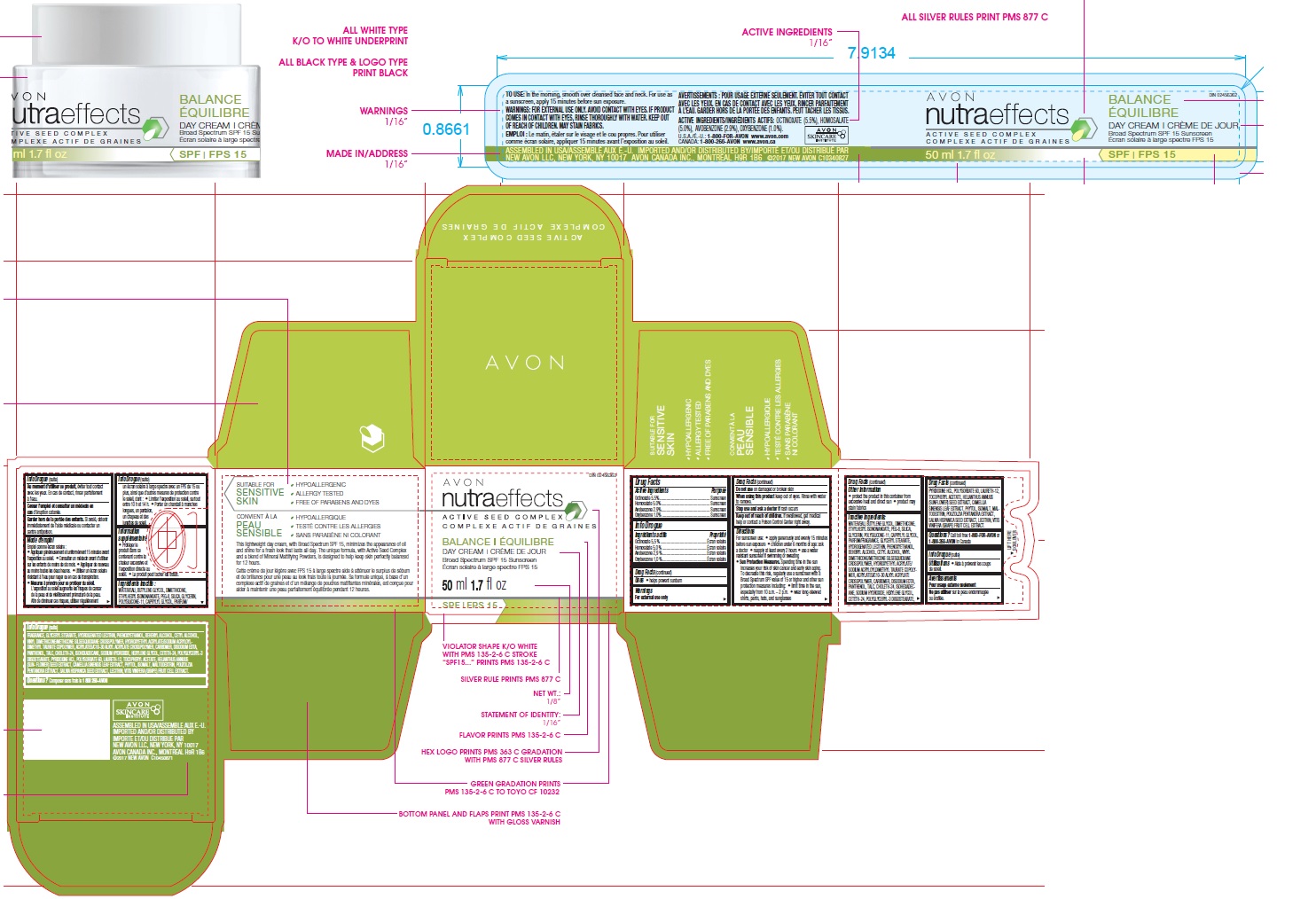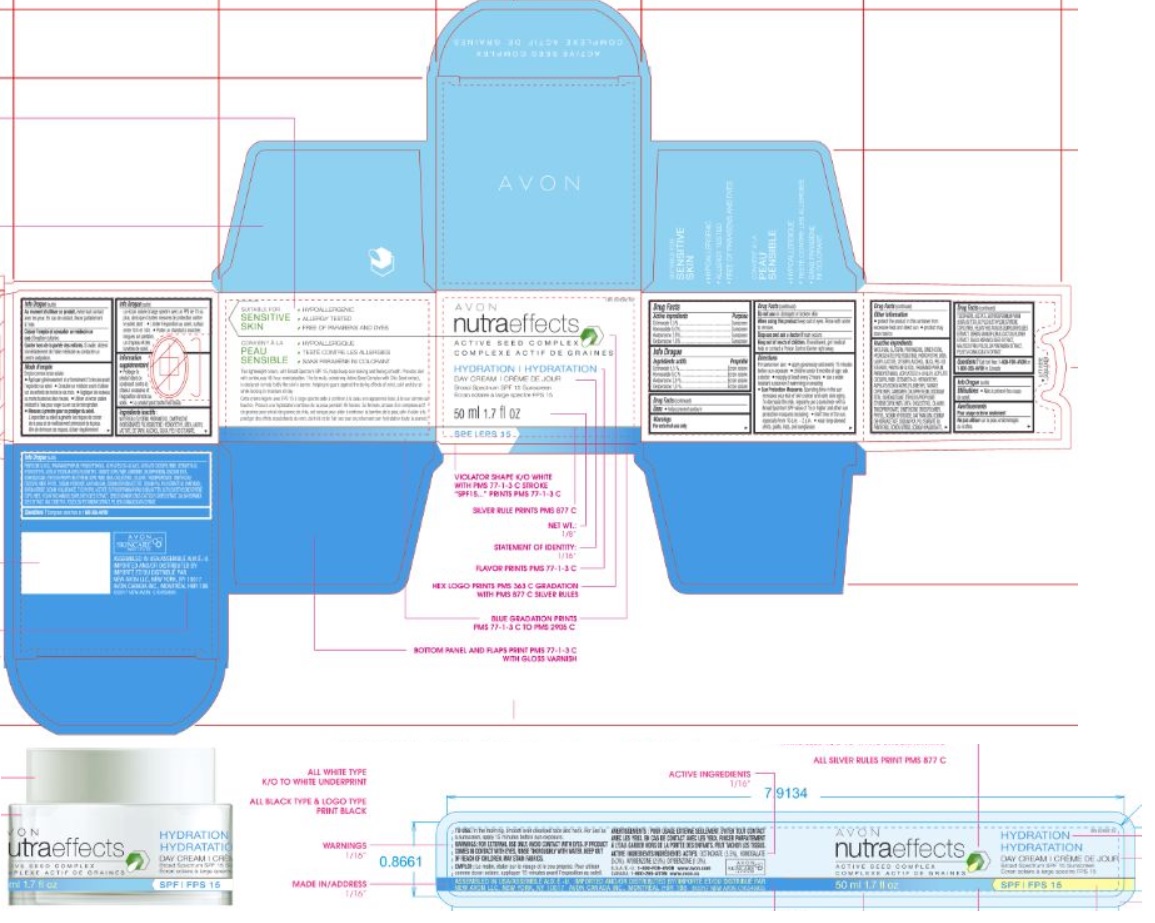 DRUG LABEL: Nutra Effects Hydration Day Cream SPF15
NDC: 10096-9503 | Form: CREAM
Manufacturer: New Avon LLC
Category: otc | Type: HUMAN OTC DRUG LABEL
Date: 20180401

ACTIVE INGREDIENTS: OCTINOXATE 5.5 g/100 g; OXYBENZONE 1 g/100 g; HOMOSALATE 5 g/100 g; AVOBENZONE 2.9 g/100 g
INACTIVE INGREDIENTS: WATER

Nutra Effects Hydration Day Cream SPF15

ACTIVE INGREDIENT

Active Ingredients/Ingrédients actifs:

OCTINOXATE (5.5 %), HOMOSALATE (5.0 %), AVOBENZONE (2.9 %), OXYBENZONE (1.0 %).

INDICATIONS & USAGE

Uses

- helps prevent sunburn

WARNINGS

For external use only

Do not use on damaged or broken skin

When using this product keep out of eyes. Rinse with water to remove.

Stop use and ask a doctor if rash occurs

Keep out of reach of children. If swallowed, get medical help or contact a Poison Control Center right away.

DOSAGE & ADMINISTRATION

Directions

For sunscreen use:

- apply generously and evenly 15 minutes before sun exposure
- children under 6 months of age: ask a doctor
- reapply at least every 2 hours
- use a water resistant sunscreen if swimming or sweating

Sun Protection Measures. Spending time in the sun increases your risk of skin cancer and early skin aging. To decrease this risk, regularly use a sunscreen with a Broad Spectrum SPF value of 15 or higher and other sun protection measures including:

- limit time in the sun, especially from 10 a.m. – 2 p.m.
- wear long-sleeved shirts, pants, hats, and sunglasses

Other Information

- protect the product in this container from excessive heat and direct sun
- product may stain fabrics

INACTIVE INGREDIENT

Inactive Ingredients/Ingrédients inactifs: WATER/EAU, GLYCERIN, PROPANEDIOL, DIMETHICONE, HYDROGENATED POLYISOBUTENE, HYDROXYETHYL UREA, LAURYL LACTATE, CETEARYL ALCOHOL, SILICA, PEG-100 STEARATE, PENTYLENE GLYCOL, FRAGRANCE/PARFUM, PHENOXYETHANOL, ACRYLATES/C10-30 ALKYL ACRYLATE CROSSPOLYMER, CETEARETH-20, HYDROXYETHYL ACRYLATE/SODIUM ACRYLOYLDIMETHYL TAURATE COPOLYMER, CARBOMER, CHLORPHENESIN, DISODIUM EDTA, ISOHEXADECANE, ETHYLENE/PROPYLENE/STYRENE COPOLYMER, UREA, CHOLESTEROL, DILAURYL THIODIPROPIONATE, DIMETHICONE CROSSPOLYMER, PHYTOL, SODIUM HYDROXIDE, XANTHAN GUM, SODIUM DEHYDROACETATE, SODIUM PCA, POLYSORBATE 60, PANTHENOL, BORON NITRIDE, SODIUM HYALURONATE, TOCOPHERYL ACETATE, BUTYROSPERMUM PARKII (SHEA) BUTTER, BUTYLENE/ETHYLENE/STYRENE COPOLYMER, HELIANTHUS ANNUUS (SUNFLOWER) SEED EXTRACT, CEREUS GRANDIFLORUS (CACTUS) FLOWER EXTRACT, SALVIA HISPANICA SEED EXTRACT, MALTODEXTRIN, POUZOLZIA PENTANDRA EXTRACT, PELVETIA CANALICULATA EXTRACT.

QUESTIONS

Questions or Comments?
Call toll free 1-800-FOR-AVON or 1-800-265-AVON in Canada